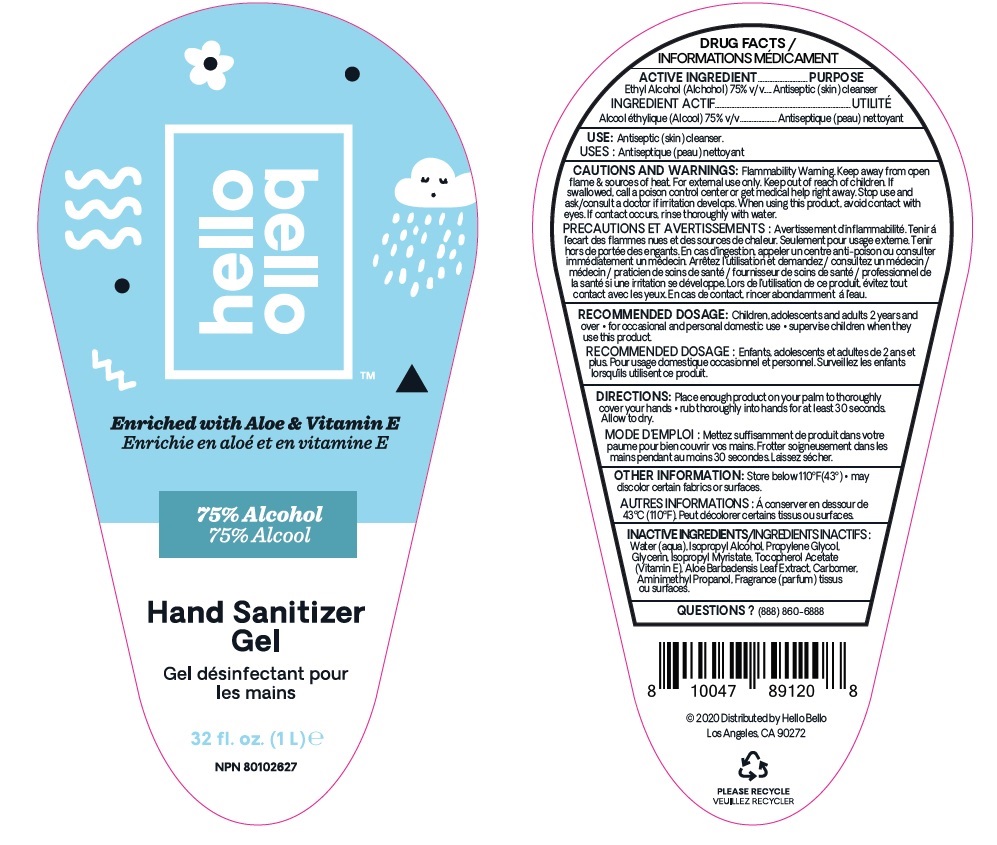 DRUG LABEL: Hello Bello Hand Sanitizer
NDC: 50157-225 | Form: GEL
Manufacturer: Brands International Corporation
Category: otc | Type: HUMAN OTC DRUG LABEL
Date: 20211223

ACTIVE INGREDIENTS: ALCOHOL 75 mL/100 mL
INACTIVE INGREDIENTS: ALOE VERA LEAF; ISOPROPYL MYRISTATE; ISOPROPYL ALCOHOL; PROPYLENE GLYCOL; WATER; GLYCERIN; .ALPHA.-TOCOPHEROL ACETATE; AMINOMETHYLPROPANOL; CARBOMER HOMOPOLYMER, UNSPECIFIED TYPE

Hello Bello Hand Sanitizer

This is a hand sanitizer manufactured according to the Temporary Policy for Preparation of Certain Alcohol-Based Hand Sanitizer Products During the Public Health Emergency (CoViD-19); Guidance for Industry.

The hand sanitizer is manufactured using only the following United States Pharmacopoeia (USP) grade ingredients in the preparation of the product (percentage in final product formulation) consistent with World Health Organization (WHO) recommendations:

1. Alcohol (ethanol) (USP or Food Chemical Codex (FCC) grade) (80%, volume/volume (v/v)) in an aqueous solution denatured according to Alcohol and Tobacco Tax and Trade Bureau regulations in 27 CFR part 20.
2. Glycerol
3. Hydrogen peroxide
4. Sterile distilled water or boiled cold water.

The firm does not add other active or inactive ingredients. Different or additional ingredients may impact the quality and potency of the product.

Active Ingredient(s)

Alcohol 75% v/v

Purpose

Antiseptic Skin Cleanser

Use

Antiseptic (skin) Cleanser

Warnings

For external use only. Flammable. Keep away from heat or flame

Do not use

Children adolescents and adults 2 years and over

Other information

- Store below 43 degree Celcius/ 100 degree F
- May discolor certain fabrics or surfaces

When using this product keep out of eyes, ears, and mouth. In case of contact with eyes, rinse eyes thoroughly with water.

Stop use and ask a doctor if irritation or rash occurs. These may be signs of a serious condition.

Keep out of reach of children. If swallowed, get medical help or contact a Poison Control Center right away.

Directions

- Place enough product on your palm to thoroughly cover your hands.
- Rub thoroughly into hands for at least 30 seconds. Allow to dry

Inactive ingredients

Glycerin, Water, Isopropyl Alcohol, Propylene Glycol, Tocopherol Acetate (Vitamin E), Aloe Barbadensis Leaf Extract, Carbomer, Aminomethyl Propanol, Parfum